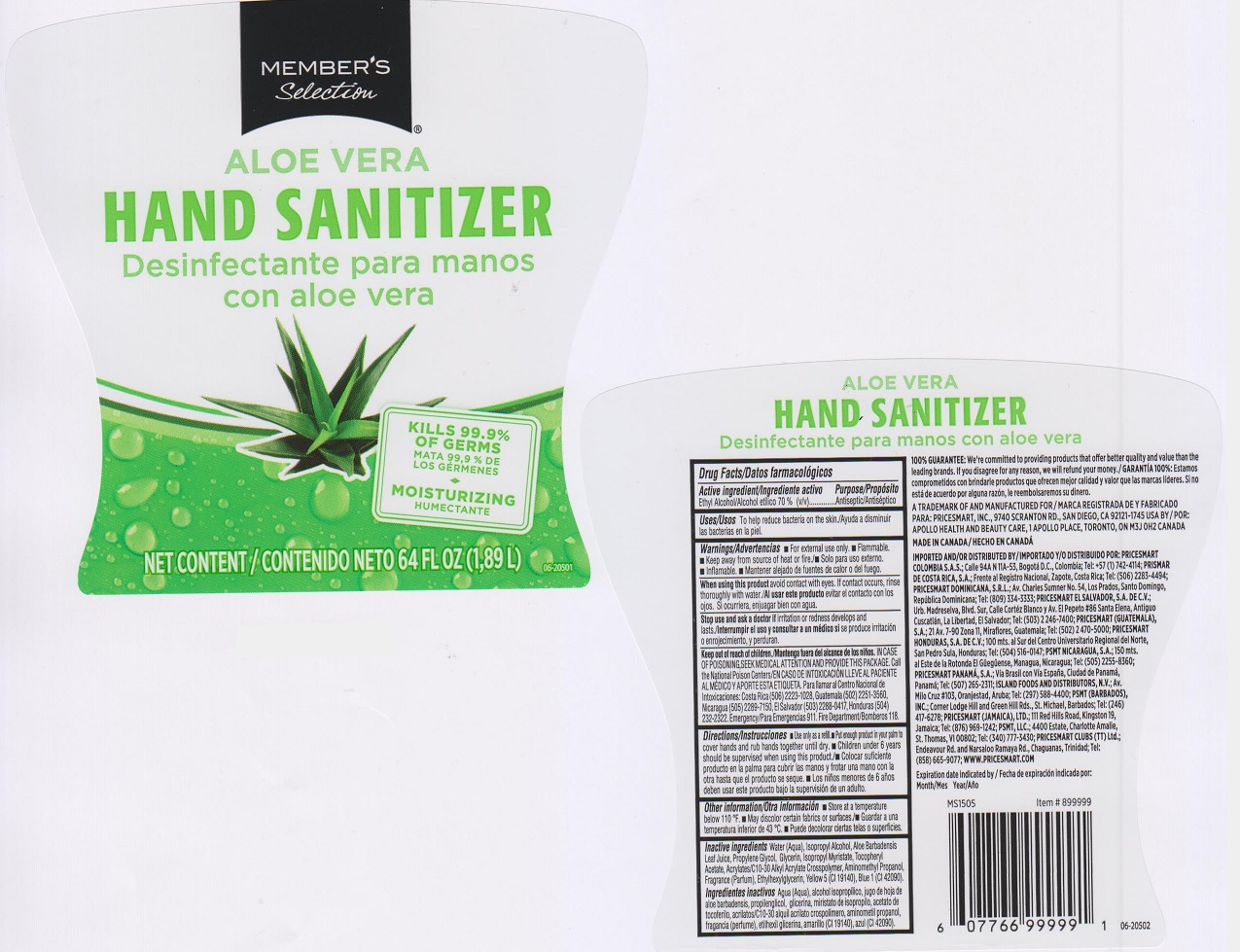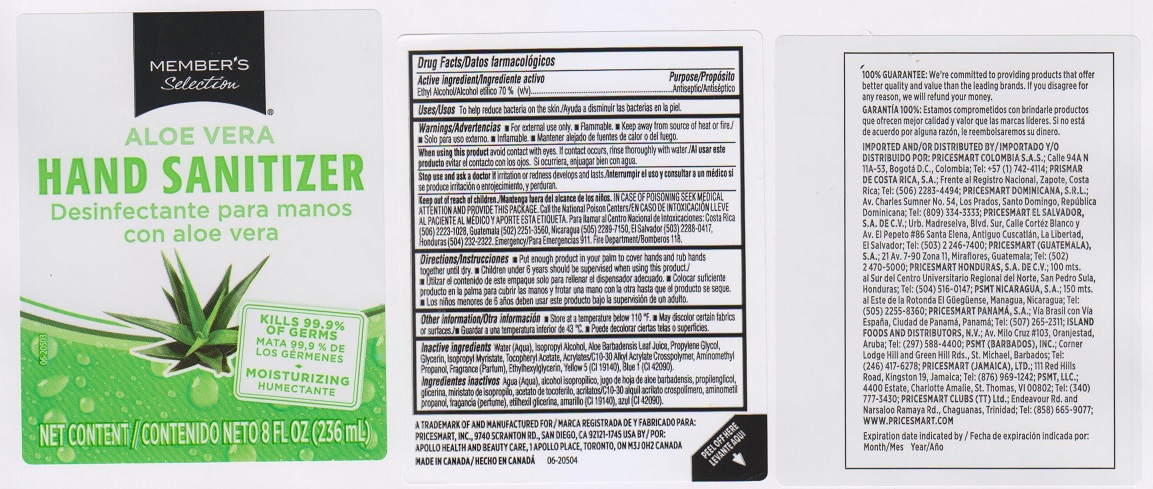 DRUG LABEL: MEMBERS SELECTION ALOE VERA SANITIZER
NDC: 63148-080 | Form: LIQUID
Manufacturer: APOLLO HEALTH AND BEAUTY CARE
Category: otc | Type: HUMAN OTC DRUG LABEL
Date: 20150709

ACTIVE INGREDIENTS: ALCOHOL 700 mg/1 mL
INACTIVE INGREDIENTS: WATER; ISOPROPYL ALCOHOL; ALOE VERA LEAF; PROPYLENE GLYCOL; GLYCERIN; ISOPROPYL MYRISTATE; .ALPHA.-TOCOPHEROL ACETATE, DL-; CARBOMER COPOLYMER TYPE A (ALLYL PENTAERYTHRITOL CROSSLINKED); AMINOMETHYLPROPANOL; ETHYLHEXYLGLYCERIN; FD&C YELLOW NO. 5; FD&C BLUE NO. 1

DRUG FACTS

Active ingredient/Ingrediente activo

Ethyl Alcohol/Alcohol etilco 70% (v/v)

Purpose/Proposito

Antiseptic/Antiséptico

Uses/Usos

to help reduce bacteria on the skin./Ayuda a disminuir las bacterias en la piel.

Warnings/Advertencias

- For external use only.
- Flammable.
- Keep away from source of heat or fire./
- Solo para uso externo.
- Inflamable.
- Mantener alejado de fuentes de calor o del fuego.

When using this product/Al usar este producto

avoid contact with eyes. If contact occurs, rinse thoroughly with water./evitar el contacto con los ojos. Si ocurriera, enjuagar bien con agua.

Stop use and ask a doctor if/Interrumpir el uso y consultar a un médico si se

irritation or redness develops and lasts./ se produce irritación o enrojecimiento, y perduran.

Keep out of reach of children./Mantenga fuera del alcance de los niños.

In case of poisoning, seek medical attention and provide this package. Call the National Poison Centers./En caso de intoxicación lleve al paciente al médico y aporte esta etiqueta. Para llamara al Centro Nacional de intoxicaciones: Cosa Rica (506) 2223-1028, Guatemala (502) 2251-3560, Nicaragua (505) 2289-7150, El Salvador (503) 2288-0417, Honduras (504) 232-2322. Emergency/Para Emergencias 911. Fire Department/Bomberos 118.

Directions/Instrucciones

- Use only as a refill. Put enough product in your palm to cover hands and rub hands together until dry./Colocar suficiente producto en la palma para cubrir las manos y frotar una mano con la otra hasta que el producto se seque.
- Children under 6 years should be supervised when using this product./Los niños menores de 6 años deben usar este producto bajo la supervisión de un adulto.

Other information/Otera información

- Store at temperature below 110°F./Guardar a una temperatura inferior de 43°C.
- May discolor certain fabrics or surfaces./Puede decolorar ciertas telas o superficies.

Inactive ingredients/Ingredients inactivos

Water (Aqua), Isopropyl Alcohol, Aloe Barbadensis Leaf Juice, Propylene Glycol, Glycerin, Isopropyl Myristate, Tocopheryl Acetate, Acrylates/C10-30 Alkyl Acrylate Crosspolymer, Aminomethyl Propanol, Fragrance (Parfum), Ethylhexylglycerin, Yellow 5 (CI 19140), Blue 1 (CI 42090).

Agua (Aqua), alcohol isopropilico, jugo de hoja de aloe barbadensis, propilenglicol, glicerina, miristato de isopropilo, acetato de tocoferilo, acrilatos/C10-30 alquil acrilatoo crospolímero, aminometil propanol, fragrancia (perfume), etilhexil gicerina, amarillo (CI 19140), azul (CI 42090).